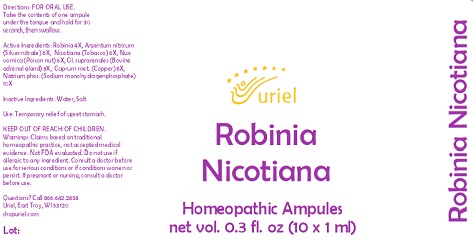 DRUG LABEL: Robinia Nicotiana
NDC: 48951-8395 | Form: LIQUID
Manufacturer: Uriel Pharmacy, Inc.
Category: homeopathic | Type: HUMAN OTC DRUG LABEL
Date: 20221012

ACTIVE INGREDIENTS: STRYCHNOS NUX-VOMICA SEED 6 [hp_X]/1 mL; COPPER 8 [hp_X]/1 mL; SILVER 6 [hp_X]/1 mL; SODIUM PHOSPHATE 10 [hp_X]/1 mL; TOBACCO LEAF 6 [hp_X]/1 mL; ROBINIA PSEUDOACACIA BARK 4 [hp_X]/1 mL; BOS TAURUS ADRENAL GLAND 8 [hp_X]/1 mL
INACTIVE INGREDIENTS: WATER; SODIUM CHLORIDE

Robinia Nicotiana

INDICATIONS AND USAGE

Directions: FOR ORAL USE.

DOSAGE AND ADMINISTRATION

Take the contents of one ampule under the tongue and hold for 30 seconds, then swallow.

ACTIVE INGREDIENT

Active Ingredients: Robinia 4X, Argentum nitricum (Silver nitrate) 6X, Nicotiana (Tobacco) 6X, Nux vomica (Poison nut) 6X,
Gl. suprarenales (Bovine adrenal gland) 8X, Cuprum met. (Copper) 8X, Natrium phos. (Sodium monohydrogenphosphate) 10X

Inactive Ingredients: Water, Salt

PURPOSE

Use: Temporary relief of upset stomach.

KEEP OUT OF REACH OF CHILDREN.

WARNINGS

Warnings: Claims based on traditional homeopathic practice, not accepted medical evidence. Not FDA evaluated. Do not use if allergic to any ingredient. Consult a doctor before use for serious conditions or if conditions worsen or persist. If pregnant or nursing, consult a doctor before use.

Questions? Call 866.642.2858
Uriel, East Troy, WI 53120
shopuriel.com Lot: